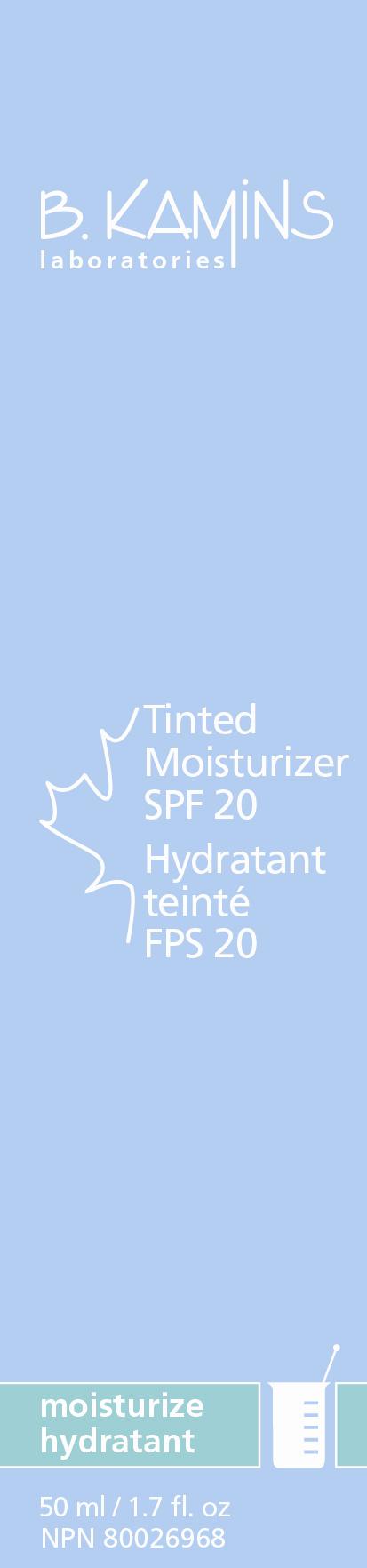 DRUG LABEL: Tinted Moisturizer SPF 20
NDC: 63550-158 | Form: CREAM
Manufacturer: Kamins Dermatologics Inc.
Category: otc | Type: HUMAN OTC DRUG LABEL
Date: 20110831

ACTIVE INGREDIENTS: ZINC OXIDE 75 mg/1 mL; TITANIUM DIOXIDE 44 mg/1 mL
INACTIVE INGREDIENTS: WATER; MEDIUM-CHAIN TRIGLYCERIDES; TRIBASIC CALCIUM PHOSPHATE; DIBUTYL ADIPATE; BUTYLENE GLYCOL; CYCLOMETHICONE 5; TRIETHOXYCAPRYLYLSILANE; LAURYL GLUCOSIDE; GLYCERIN; XANTHAN GUM; MAGNESIUM ALUMINUM SILICATE; ACAI OIL; CITRIC ACID MONOHYDRATE; ISONONYL ISONONANOATE; WHITE WAX; PHENOXYETHANOL; CAPRYLYL GLYCOL; SORBIC ACID; FERRIC OXIDE RED; FERRIC OXIDE YELLOW

Tinted Moisturizer SPF 20 CONSUMER LABELING

Active ingredients:

Zinc Oxide 7.5%

Titanium Dioxide 4.4%

Purpose: Sunscreen

Keep out of reach of children.

INDICATIONS AND USAGE

This cream is enriched with moisturizing acai oil to help skin remain hydrated while adding a touch of color and glow to your skin.

Uses
■ Helps prevent sunburn.

■ Higher SPF gives more sunburn protection.

■ Provides moderate protection against sunburn.

Warnings
■ For external use only.
■ When using this product, keep out of eyes. If contact occurs, rinse abundantly with water to remove.
■ Stop use and ask a doctor if rash or irritation develops and lasts.
■ If swallowed, seek medical assistance or contact a Poison Control Center immediately.

Directions

■ Apply in the morning and prior to sun exposure. Reapply as needed.
■ Children under 6 months of ask: ask a doctor.

INACTIVE INGREDIENT

Inactive ingredients: Aqua/Water/Eau, Caprylic/Capric Triglyceride, Oleyl Oleate, Polyglyceryl-2 Dipolyhydroxystearate, Pentaerythrityl Tetraisostearate, Butylene Glycol, Cyclopentasiloxane, PEG/PPG-20/15 Dimethicone, Triethoxycaprylylsilane, Sodium Lauryl Glucose Carboxylate, Lauryl Glucoside, Glycerin, Xanthan gum, Magnesium Aluminum Silicate, Acai Fruit Oil, Citric Acid, Isononyl Isononanoate, Isopropyl Titanium Triisostearate, Synthetic Wax, Caprylyl Glycol, Phenoxyethanol, Sorbic Acid, Iron oxides (CI 77491, 77492).

PACKAGE LABEL

B. KAMINS

TINTED MOISTURIZER SPF15

50mL / 1.7 fl.oz

NPN 80026968

image/jpg